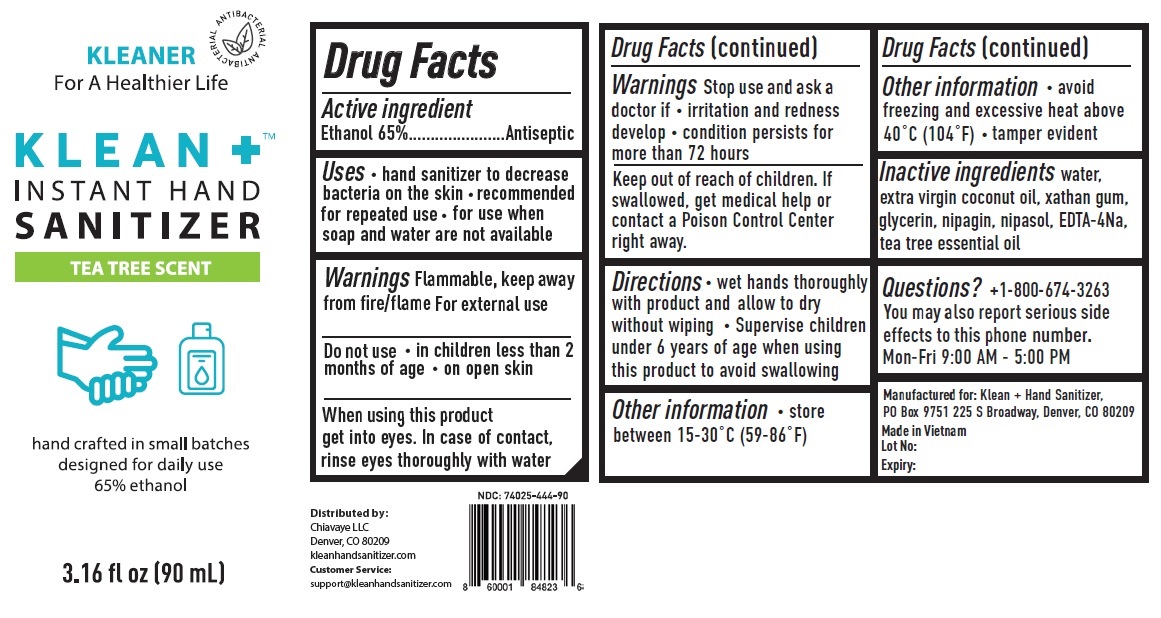 DRUG LABEL: KLEAN PLUS INSTANT HAND SANITIZER TEA TREE SCENT
NDC: 74025-444 | Form: GEL
Manufacturer: CATCHERS INTERNATIONAL LIMITED LIABILITY COMPANY
Category: otc | Type: HUMAN OTC DRUG LABEL
Date: 20200407

ACTIVE INGREDIENTS: ALCOHOL 65 mL/100 mL
INACTIVE INGREDIENTS: WATER; COCONUT OIL; XANTHAN GUM; GLYCERIN; METHYLPARABEN SODIUM; PROPYLPARABEN; EDETATE SODIUM; TEA TREE OIL

KLEAN +TM INSTANT HAND SANITIZER TEA TREE SCENT

Active ingredient

Ethanol 65%

Purpose

Antiseptic

INDICATIONS AND USAGE

Uses • hand sanitizer to decrease bacteria on the skin • recommended for repeated use • for use when soap and water are not available

Warnings Flammable, keep away from fire/flame

For external use

Do not use • in children less than 2 months of age • on open skin

When using this product get into eyes. In case of contact, rinse eyes thoroughly with water

Stop use and ask a doctor if • irritation and redness develop • condition persists for more than 72 hours

Keep out of reach of children. If swallowed, get medical help or contact a Poison Control Center right away.

DOSAGE AND ADMINISTRATION

Directions • wet hands thoroughly with product and allow to dry without wiping • Supervise children under 6 years of age when using this product to avoid swallowing

Other information • store between 15-30°C (59-86°F) • avoid freezing and excessive heat above 40°C (104°F) • tamper evident

INACTIVE INGREDIENT

Inactive ingredients water, extra virgin coconut oil, xanthan gum, glycerin, nipagin, nipasol, EDTA-4Na, tea tree essential oil

Questions? +1-800-674-3263
You may also report serious side effects to this phone number.

Mon-Fri 9:00 AM - 5:00 PM

KLEANER For A Healthier Life

ANTIBACTERIAL

TEA TREE SCENT

hand crafted in small batches designed for daily use

Distributed by:

Chiavaye LLC

Denver, CO 80209

kleanhandsanitizer.com

Customer Service:

support@kleanhandsanitizer.com

Manufactured for: Klean + Hand Sanitizer, PO Box 9751 225 S Broadway, Denver, CO 80209

Made in Vietnam